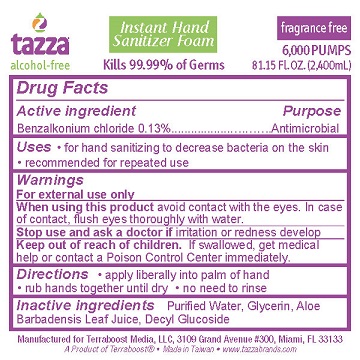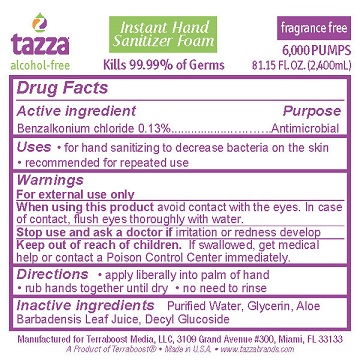 DRUG LABEL: Hand Sanitizer
NDC: 76370-0006 | Form: LIQUID
Manufacturer: Tazza Brands East Inc.
Category: otc | Type: HUMAN OTC DRUG LABEL
Date: 20250101

ACTIVE INGREDIENTS: BENZALKONIUM CHLORIDE 0.13 g/100 mL
INACTIVE INGREDIENTS: WATER; GLYCERIN; ALOE VERA LEAF; DECYL GLUCOSIDE

TAZZA INSTANT HAND SANITIZER FOAM

Drug Facts

Active ingredient

Benzalkonium chloride 0.13%

Purpose

Antimicrobial

Uses

- for hand sanitizing to decrease bacteria on the skin
- recommended for repeated use

Warnings

For external use only

When using this product avoid contact with the eyes. In case of contact, flush eyes with water.

Stop use and ask a doctor if irritation or redness develop

Keep out of reach of children. If swallowed, get medical help or contact a Poison Control Center immediately.

Directions

- apply liberally into palm of hand
- rub hands together until dry
- no need to rinse

Inactive ingredients

Purified Water, Glycerin, Aloe Barbadensis Leaf Juice, Decyl Glucoside

Manufactured for Terraboost Media, LLC, 3109 Grand Avenue #300, Miami, FL 33133

A Product of Terraboost®

Made in Taiwan [Made in U.S.A.]

www.tazzabrands.com

PACKAGE LABEL

Tazza Instant Hand Sanitizer Foam

alcohol-free

Kills 99.99% of Germs

fragrance free

2,500 PUMPS

33.81 Fl. OZ. (1,000mL)